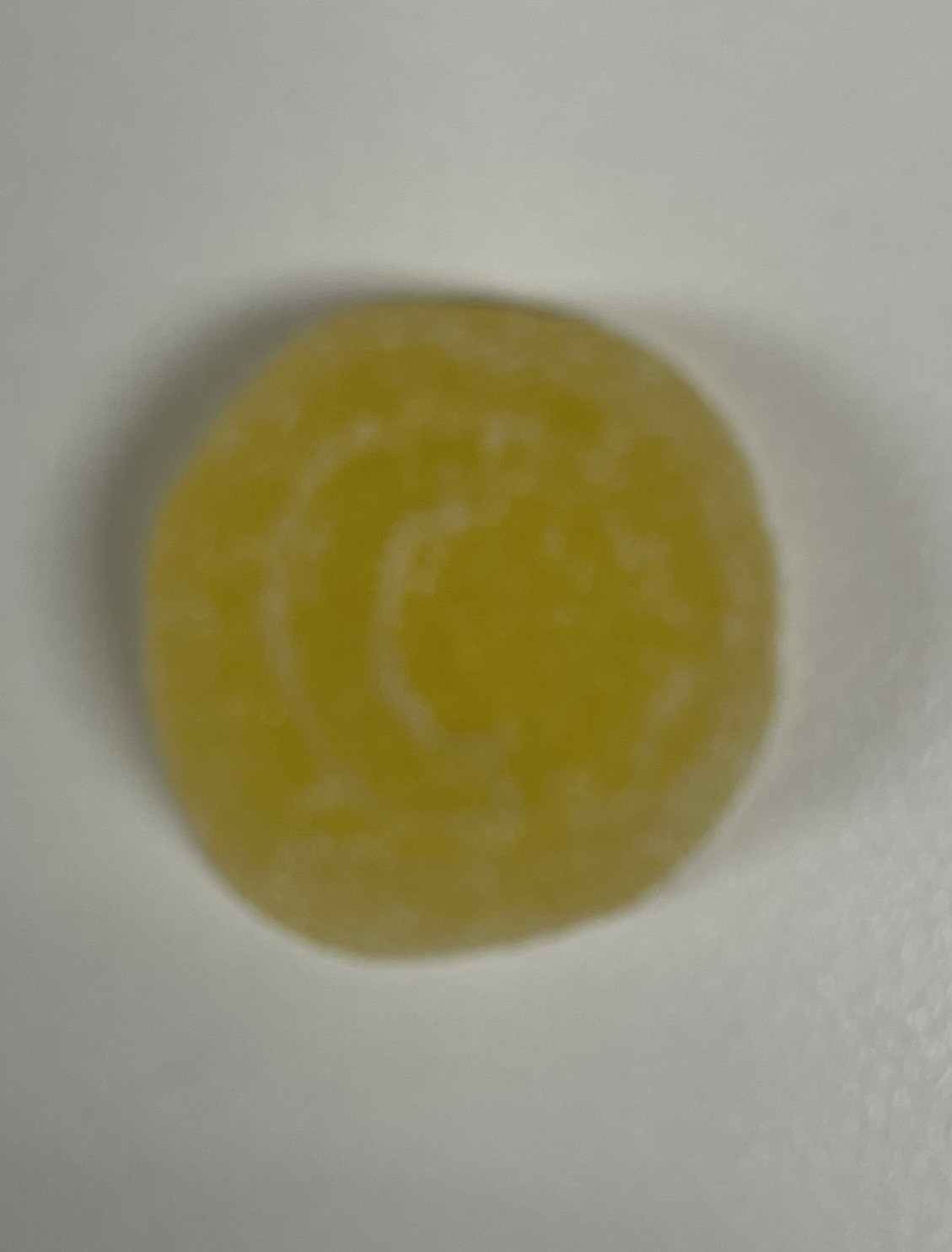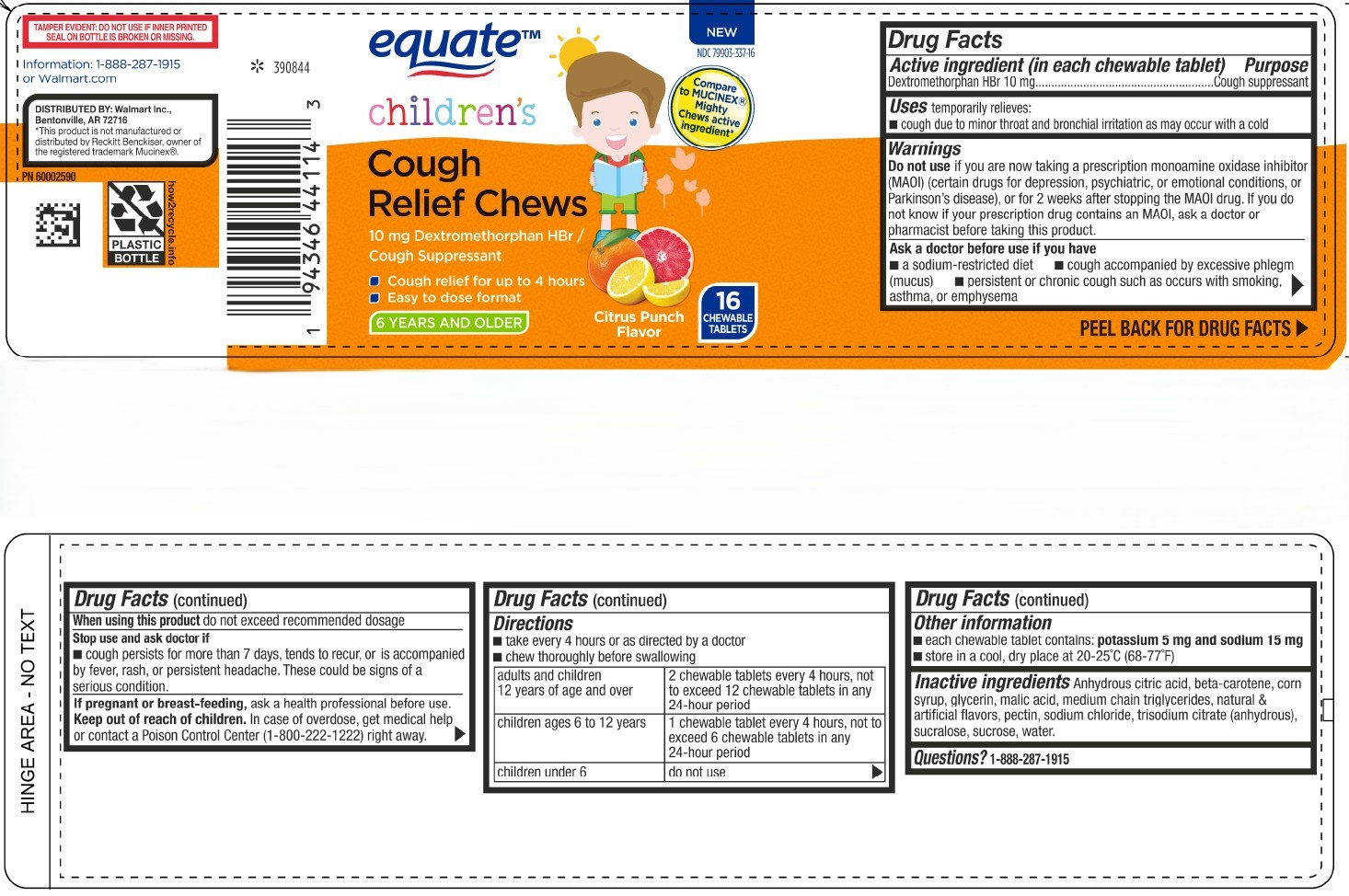 DRUG LABEL: Equate Kids Daytime Dex Cough Gels
NDC: 79903-337 | Form: TABLET, CHEWABLE
Manufacturer: Walmart
Category: otc | Type: HUMAN OTC DRUG LABEL
Date: 20250609

ACTIVE INGREDIENTS: DEXTROMETHORPHAN HYDROBROMIDE 10 mg/1 1
INACTIVE INGREDIENTS: WATER

Dextromethorphan HBr 10 mg

Active ingredient (in each chewable tablet)

Dextromethorphan HBr 10 mg

Purpose

Cough suppressant

INDICATIONS AND USAGE

Uses temporarily relieves:

- cough due to minor throat and bronchial irritation as may occur with a cold

Warnings

Do not use if you are now taking a prescription monoamine axidase inhibitor (MAOI) (certain drugs for depression, psychiatric, or emotional conditions, or Parkinson's disease), or for 2 week after stopping the MAOI drug. If you do not know if your prescription drug contains an MAOI, ask a doctor or pharmacist before taking this product.

Ask a doctor before use if you have

- a sodium-restricted diet
- cough accompanied by excessive phlegm (mucus)
- persistent or chronic cough such as occurs with smoking, asthma, or emphysema

When using this product do not exceed recommended dosage

Stop use and ask doctor if

- cough persists for more than 7 days, tends to recur, or is accompanied by fever, rash, or persistent headache. These could be signs of a serious condition.

PREGNANCY OR BREAST FEEDING

If pregnant or breast-feeding, ask a health professional before use.

Keep out of reach of children.

OVERDOSAGE

In case of overdose, get medical help or contact a Poison Control Center (1-800-222-1222) right away.

Directions

- take every 4 hours or as directed by a doctor
- chew thoroughly before swallowing

adults and children 12 years of age and over - 2 chewable tablets every 4 hours, not to exceed 12 chewable tablets in any 24-hour period

children ages 6 to 12 years - 1 chewable tablet every 4 hours, not to exceed 6 chewable tablets in any 24-hour period

children under 6 - do not use

Other information

- each chewable tablet contains: potassium 5 mg and sodium 15 mg
- store in a cool, dry place at 20° - 25°C (68° to 77°F)

INACTIVE INGREDIENT

Inactive ingredients: Anhydrous citric acid, beta-carotene, corn syrup, glycerin, malic acid, medium chain triglycerides, natural & artificial flavors, pectin, sodium chloride, trisodium citrate (anhydrous), sucralose, sucrose, water.

Questions? 1-888-287-1915